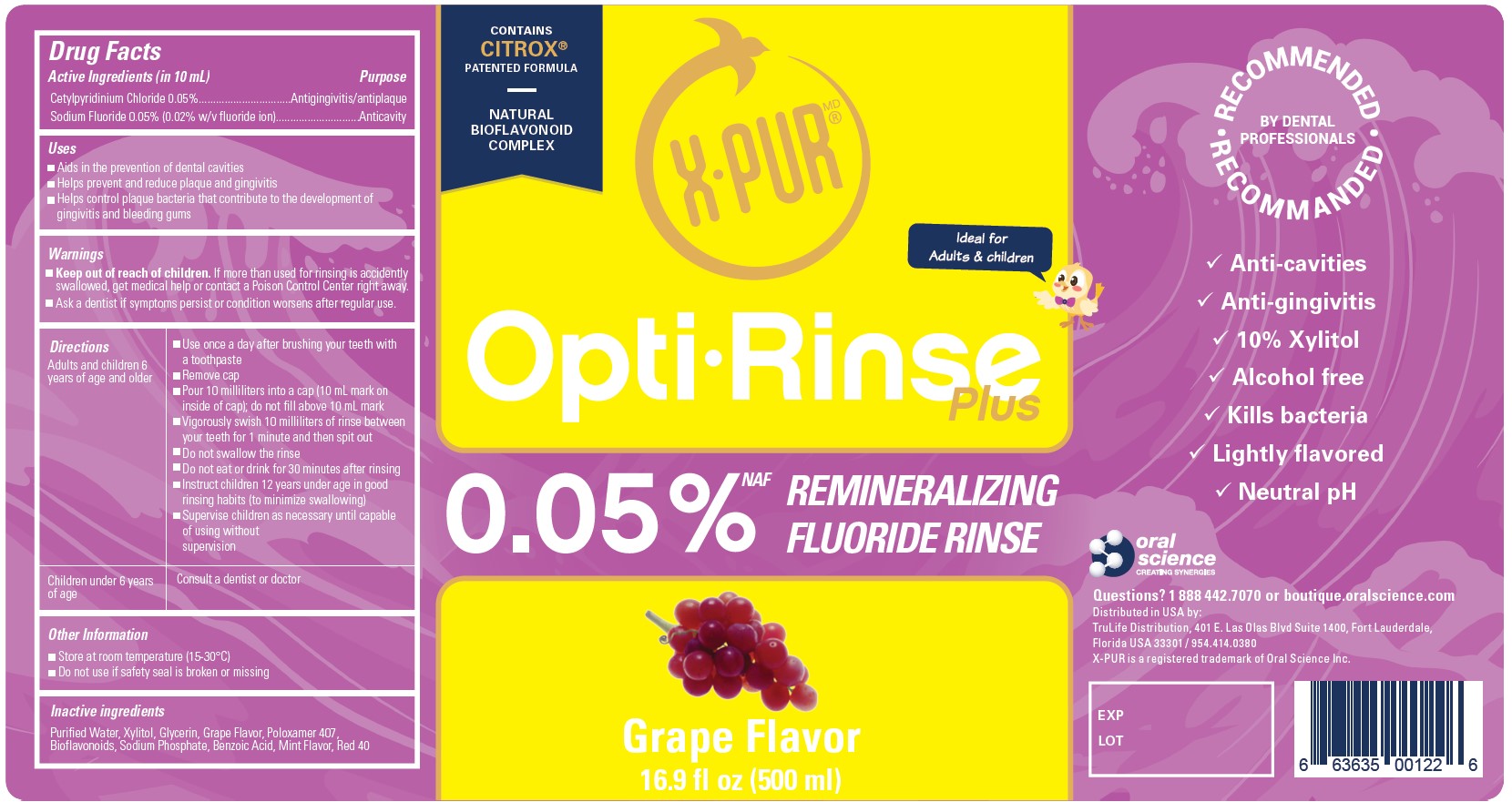 DRUG LABEL: OptiRinse Plus
NDC: 77982-001 | Form: LIQUID
Manufacturer: Laboratoires MSP Inc
Category: otc | Type: HUMAN OTC DRUG LABEL
Date: 20201106

ACTIVE INGREDIENTS: CETYLPYRIDINIUM CHLORIDE 0.05 mg/1 mL; SODIUM FLUORIDE 0.05 mg/1 mL
INACTIVE INGREDIENTS: WATER; XYLITOL; GLYCERIN; METHYL ANTHRANILATE; POLOXAMER 407; CITRUS BIOFLAVONOIDS; SODIUM PHOSPHATE; BENZOIC ACID; PULEGONE; FD&C RED NO. 40

OptiRinse Plus

Active Ingredients (in 10 mL)

Cetylpyridinum Chloride 0.05%

Sodium Fluoride 0.05% (0.02% w/v fluoride ion)

Purpose

Antigingivitis/antiplaque

Anticavity

Uses

- Aids in the prevention of dental cavities
- Helps prevent and reduce plaque and gingivitis
- Helps control plaque bacteria that contribute to the development of gingivitis and bleeding gums

Warnings

- Keep out of reach of children. If more than used for rinsing is accidentally swallowed, get medical help or contact a Poison Control Center right away.

WARNINGS

- Ask a dentist if symptoms persist or condition worsens after regular use.

Directions

Adults and children 6 years of age and older | - Use once a day after brushing your teeth with a toothpaste - Remove cap - Pour 10 milliliters into a cap (10 mL mark on inside of cap); do not fill above 10 mL mark - Vigorously swish 10 milliliters of rinse between your teeth for 1 minute and then spit out - Do not swallow the rinse - Do not eat or drink for 30 minutes after rinsing - Instruct children 12 years under age in good rinsing habits (to minimize swallowing) - Supervise children as necessary until capable of using without supervision
Children under 6 years of age | Consult a dentist or doctor

Other Information

- Store at room temperature (15-30°C)
- Do not use if safety seal is broken or missing

Inactive Ingredients

Purified Water, Xylitol, Glycerin, Grape Flavor, Poloxamer 407, Bioflavonoids, Sodium Phosphate, Benzoic Acid, Mint Flavor, Red 40

OptiRinse Plus - Grape - 500 mL - NDC 77982-001-01

OptiRinse Plus

Contains Citrox patented formula

Natural Bioflavinoid Complex

Ideal for Adults & children

00.05% NAF Remineralizing Fluoride Rinse

Grape Flavor

16.9 fl oz (500 ml)

Recommended by Dental Professionals

- Anti-cavities
- Anti-gingivitis
- 10% Xylitol
- Alcohol free
- Kills bacteria
- Lightly flavored
- Neutral pH

Questions? 1 888 442.7070 or boutique.oralscience.com

Distributed in USA by:

TruLife Distribution, 401 E Las Olas Blvd Suite 1400, Fort Lauderdale,

Floirida USA 33301 / 954.414.0380

X-PUR is a registered trademark of Oral Science Inc.